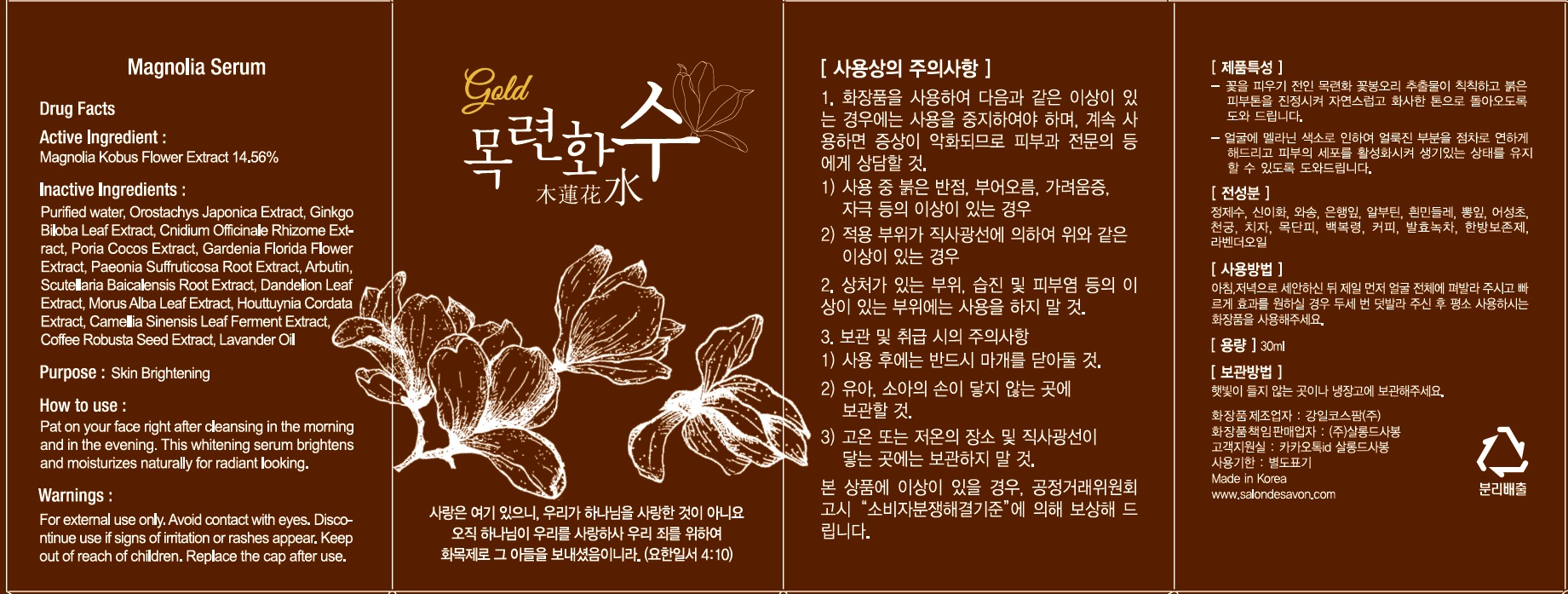 DRUG LABEL: Magnolia Serum
NDC: 70800-100 | Form: LIQUID
Manufacturer: Salon de Savon
Category: otc | Type: HUMAN OTC DRUG LABEL
Date: 20191210

ACTIVE INGREDIENTS: MAGNOLIA KOBUS FLOWERING TOP 4.36 g/30 mL
INACTIVE INGREDIENTS: Water; Arbutin

ACTIVE INGREDIENT

Active Ingredient: Magnolia Kobus Flower Extract 14.56%

INACTIVE INGREDIENT

Inactive Ingredients:

Purified water, Orostachys Japonica Extract, Ginkgo Biloba Leaf Extract, Cnidium Officinale Rhizome Extract, Poria Cocos Extract, Gardenia Florida Flower Extract, Paeonia Suffruticosa Root Extract, Dandelion Leaf Extract, Morus Alba Leaf Extract,
Houttuynia Cordata Extract, Arbutin, Scutellaria Baicalensis Root Extract, Camellia Sinensis Leaf Ferment Extract, Coffee Robusta Seed Extract, Lavander Oil

PURPOSE

Purpose: Skin Brightening

WARNINGS

For external use only. Avoid contact with eyes. Discontinue use if signs of irritation or rashes appear. Keep out of reach of children. Replace the cap after use.

KEEP OUT OF REACH OF CHILDREN

How to use

Pat on your face right after cleansing in the morning and in the evening. This whitening serum brightens and monetarizes naturally for radiant looking.

How to use

Pat on your face right after cleansing in the morning and in the evening. This whitening serum brightens and monetarizes naturally for radiant looking.